DRUG LABEL: fenofibrate
NDC: 43353-248 | Form: TABLET
Manufacturer: Food and Drug Administration
Category: other | Type: INDEXING - WARNING LETTER ALERT
Date: 20171205

ACTIVE INGREDIENTS: FENOFIBRATE 48 mg/1 1

Warning Letter

https://www.fda.gov/ICECI/EnforcementActions/WarningLetters/2017/ucm588722.htm